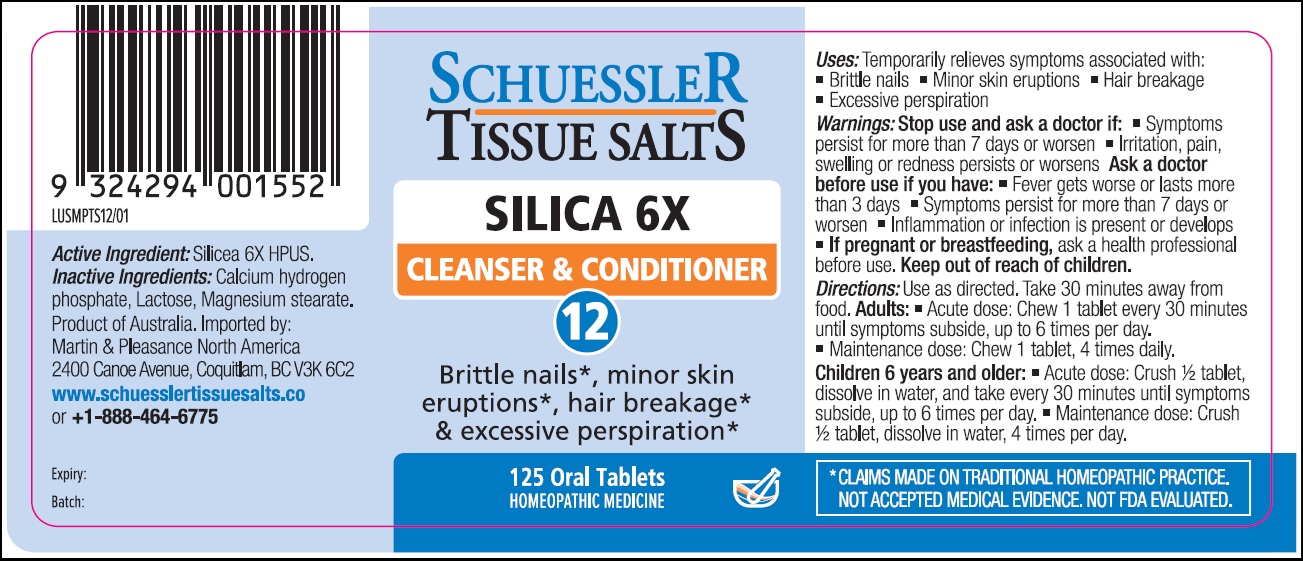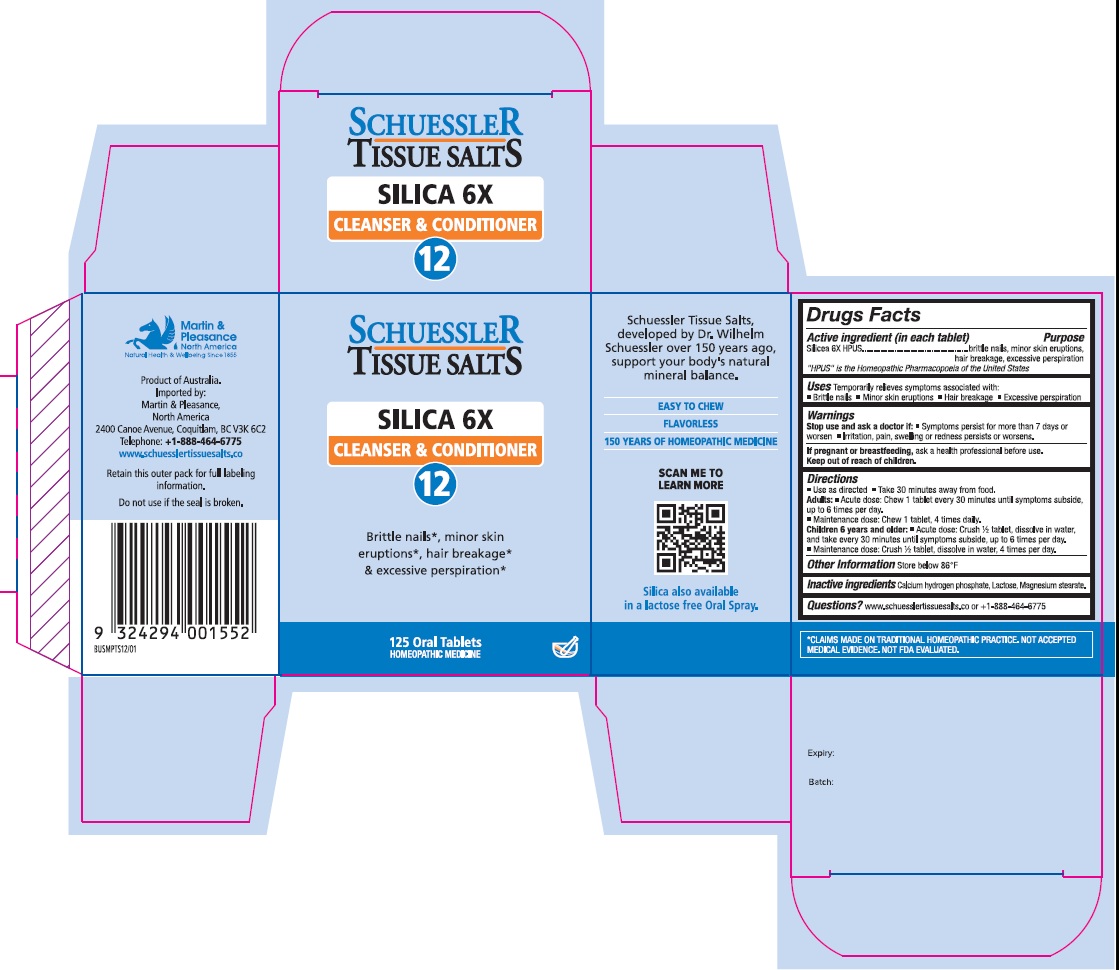 DRUG LABEL: Schuessler Tissue Salts Silica Cleanser and Conditioner 12
NDC: 84999-024 | Form: TABLET, CHEWABLE
Manufacturer: Martin & Pleasance Pty Ltd
Category: homeopathic | Type: HUMAN OTC DRUG LABEL
Date: 20250804

ACTIVE INGREDIENTS: SILICON DIOXIDE 6 [hp_X]/1 1
INACTIVE INGREDIENTS: LACTOSE MONOHYDRATE; MAGNESIUM STEARATE; ANHYDROUS DIBASIC CALCIUM PHOSPHATE

Active Ingredients Purpose

Silicea 6X HPUS brittle nails, minor skin eruptions, hair breakage, excessive perspiration

" HPUS" is the Homeopathic Pharmacopoeia of the United States

Uses

Temporarily relieves symptoms associated with

- Brittle nails
- Minor skin eruptions
- Hair breakage
- Excessive perspiration

Warnings

Stop use and ask a doctor if:

- Symptoms persist for more than 7 days or worsen
- Irritation, pain, swelling, or redness persists or worsens

If pregnant or breastfeeding, ask a health professional before use.

Keep out of reach of children.

Directions

- Use as directed
- Take 30 minutes away from food

Adults: Acute dose: Chew 1 tablet every 30 minutes until symptoms subside up to 6 times per day.

Maintenance dose: Chew 1 tablet, 4 times daily.

Children 6 years and older: Acute dose: Crush 1/2 tablet, dissolve in water, and take every 30 minutes until symptoms subside, up to six times per day.

Maintenance dose :Crush 1/2 tablet, dissolve in water, 4 times per day.

Other Information

Store below 86°F

Inactive Ingredients

Calcium hydrogen phosphate, Lactose, Magnesium stearate

Questions?www.schuesslertissuesalts.co or + 1-888-464-6775